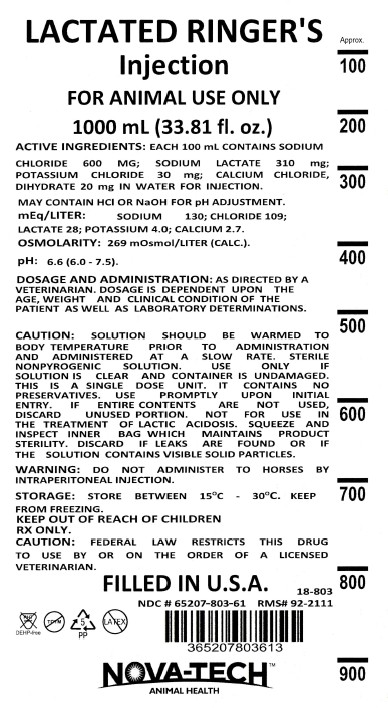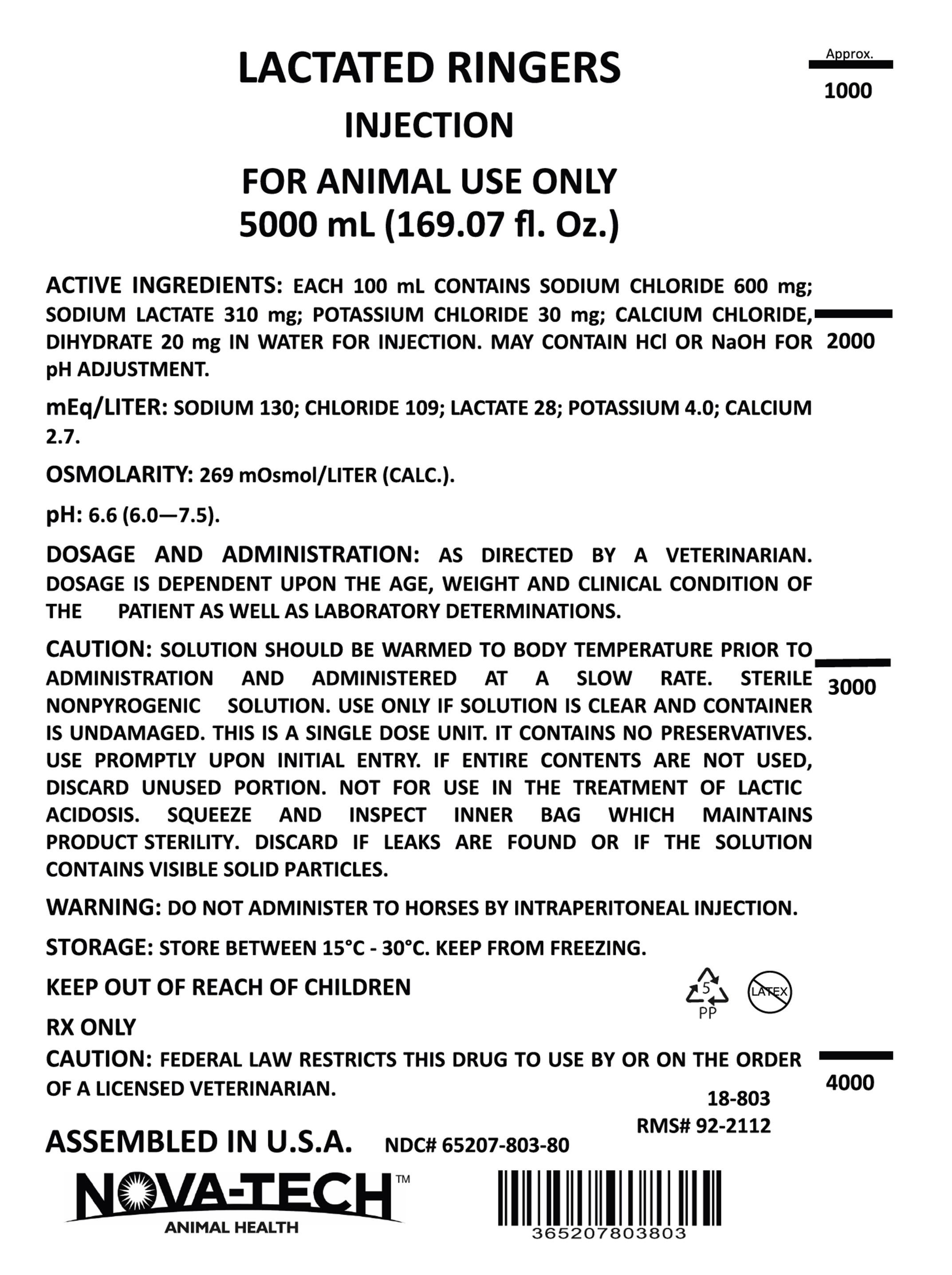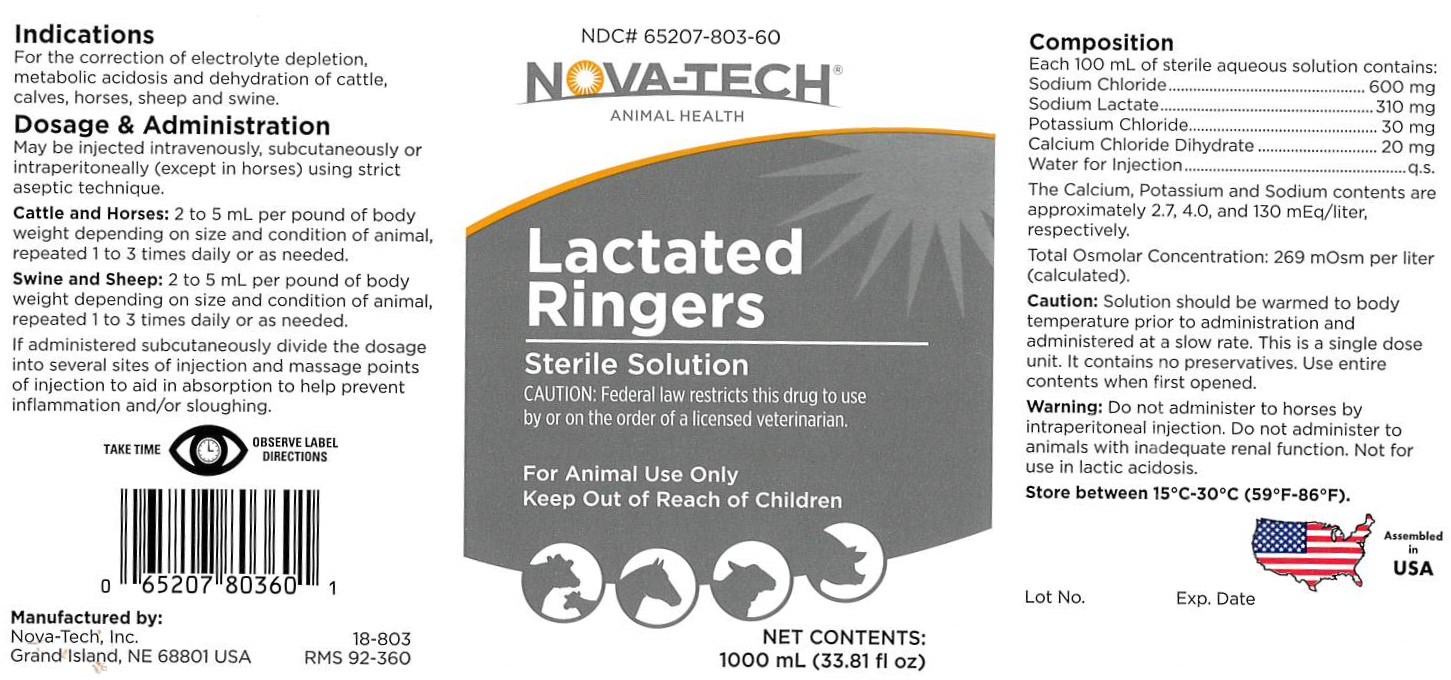 DRUG LABEL: Lactated Ringers
NDC: 65207-803 | Form: INJECTION, SOLUTION
Manufacturer: Nova-Tech, Inc.
Category: animal | Type: PRESCRIPTION ANIMAL DRUG LABEL
Date: 20251007

ACTIVE INGREDIENTS: SODIUM CHLORIDE 600 mg/100 mL; SODIUM LACTATE 310 mg/100 mL; POTASSIUM CHLORIDE 30 mg/100 mL; CALCIUM CHLORIDE 20 mg/100 mL

Lactated Ringers

Composition

Each 100 mL of sterile aquious solution contains:

Sodium Chloride ............................ 600 mg
Sodium Lactate .............................. 310 mg
Potassium Chloride .......................... 30 mg
Calcium Chloride Dihydrate ............... 20 mg
Water for Injection .............................. q.s.

The Calcium, Potassium and Sodium contents are approximately 2.7, 4.0, and 130 mEq/liter,
respectively. Total Osomolar concentration: 269 mOsm per liter (calculated).

Each 100 mL contains Sodium Chloride 600 mg; Sodium Lactate 310 mg; Potassium Chloride 30 mg; Calcium Chloride, Dihydrate 20 mg in Water for Injection.

May contain HCL or NaOH for pH adjustment.

mEq/Liter: Sodium 130; Chloride 109; Lactate 28; Potassium 4.0; Calcium 2.7.

Osomolarity: 269 mOsmol/liter (calc.).

pH: 6.6 (6.0 - 7.5).

INDICATIONS

For the correction of electrolyte depletion, metabolic acidosis and dehydration
of cattle, calves, horses, sheep and swine.

DOSAGE & ADMINISTRATION:

May be injected intravenously, subcutaneously or
intraperitoneally (except in horses) using strict aseptic technique.

Cattle and Horses: 2 to 5 mL per pound of body weight depending on size and condition
of animal, repeated 1 to 3 times daily or as needed.

Swine and Sheep: 2 to 5 mL per pound of body weight depending on size and condition
of animal, repeated 1 to 3 times daily or as needed.

If administered subcutaneously divide the dosage into several sites of injection and
massage points of injection to aid in absorption and help prevent inflammation and/or sloughing.

As directed by a veterinarian. Dosage is dependent upon the age, weight and clinical condition of the patient as well as laboratory determinations.

CAUTION:

Solution should be warmed to body temperature prior to administration and
administered at a slow rate. This is a single dose unit. It contains no preservatives. Use entire
contents when first opened.

Solution should be warmed to body temperature prior to administration and administered at a slow rate. Sterile nonpyrogenic solution. Use only if solution is clear and container is undamaged. This is a single dose unit. It contains no preservatives. Use promptly upon initial entry. If entire contents are not used, discard unused portion. Not for use in the treatment of lactic acidosis. Squeeze and inspect inner bag which maintains product sterility. Discard if leaks are found or if the solution contains visible solid particles.

WARNING:

Do not administer to horses by intraperitoneal injection. Do not administer to
animals with inadequate renal function. Not for use in lactic acidosis.

STORAGE AND HANDLING

Store between 15°C-30°C (59°F-86°F)

WARNINGS AND PRECAUTIONS

TAKE TIME OBSERVE LABEL DIRECTIONS

KEEP OUT OF REACH OF CHILDREN

RX only.

VETERINARY INDICATIONS

STERILE SOLUTION

FOR ANIMAL USE ONLY

CAUTION:

Federal law restricts this drug to use by or on the order of a licensed veterinarian.

INFORMATION FOR OWNERS/CAREGIVERS

Manufactured by:

Nova-Tech, Inc.
Grand Island, NE 68801 USA

NDC# 65207-803-60

Nova-Tech®

Animal Health

Net Contents:

1000 mL (33.81 fl oz)

Lot No.

Exp. Date

Filled in USA

DEHP-free

NDC # 65207-803-61

18-803

RMS# 92-2111

365207803613

NDC # 65207-803-80

18-803

RMS 92-2112

365207803803